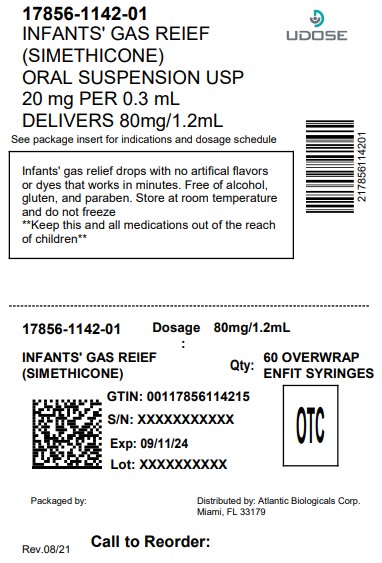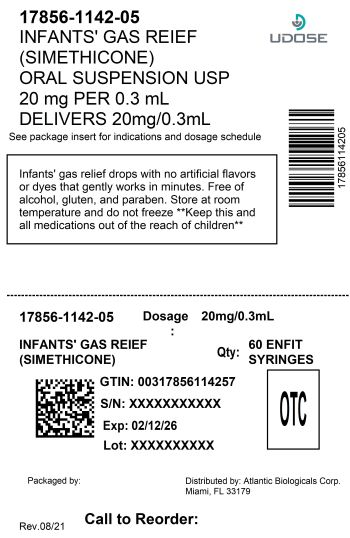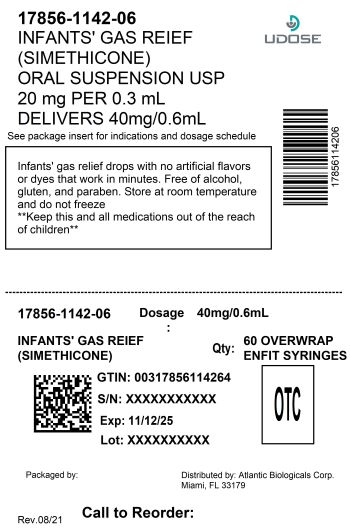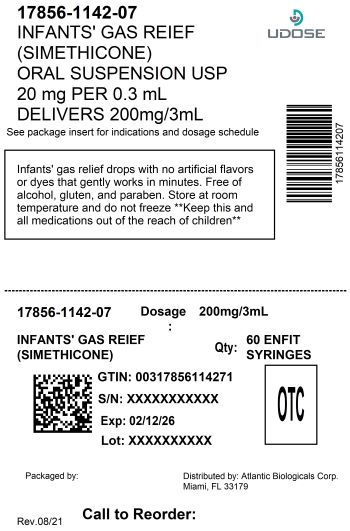 DRUG LABEL: TEENY TUMMY
NDC: 17856-1142 | Form: SUSPENSION
Manufacturer: ALTANTIC BIOLOGICAS CORP.
Category: otc | Type: HUMAN OTC DRUG LABEL
Date: 20260213

ACTIVE INGREDIENTS: DIMETHICONE 20 mg/0.3 mL
INACTIVE INGREDIENTS: CARBOXYMETHYLCELLULOSE SODIUM, UNSPECIFIED FORM; ANHYDROUS CITRIC ACID; MICROCRYSTALLINE CELLULOSE; POLYSORBATE 60; POTASSIUM SORBATE; WATER; SODIUM BENZOATE; SORBITAN MONOSTEARATE; SORBITOL; XANTHAN GUM

INFANT'S GAS RELIEF DROPS
TEENY TUMMY
fast instant gas relief
INFANT'S GAS RELIEF DROPS

Active ingredient (in each 0.3 mL)

Simethicone 20 mg

Purpose

Antigas

Uses

relieves the symptoms referred to as gas

Warnings

In case of overdose seek medical help immediately or contact Poison Control Center right away (800)222-1222

For adverse reactions contact the FDA at www.fda.gov or 1(888)463-6332

KEEP OUT OF REACH OF CHILDREN

Keep this and all medications out of the reach of children

Directions

• shake well before using
• all dosages may be repeated as needed, after meals and at bedtime, or as directed by a physician
• do not exceed 12 doses per day
• fill enclosed dropper to recommended dosage level and dispense liquid slowly into baby’s mouth, toward the inner cheek
• dosage can also be mixed with 1 oz. of cool water, infant formula or other suitable liquids
• clean dropper well after each use and replace original cap on bottle

Age (years) | Weight (lbs) | Dose
infants under 2 | under 24 | 0.3 mL
children over 2 | over 24 | 0.6 mL

Other information

- TAMPER-EVIDENT:Do not use if printed seal under cap is broken or punctured
- store at room temperature
- do not freeze
- see bottom panel for lot number and expiration date

Inactive ingredients

Carboxymethylcellulose sodium, Citric acid, Flavor strawberry, Microcrystalline cellulose, Polysorbate 60, Potassium sorbate, Purified water, Sodium benzoate, Sorbitan monostearate, Sorbitol solution, Xanthan gum.

Questions or comments ?

DISTRIBUTED BY:

ATLANTIC BIOLOGICALS CORP.

MIAMI, FL 33179